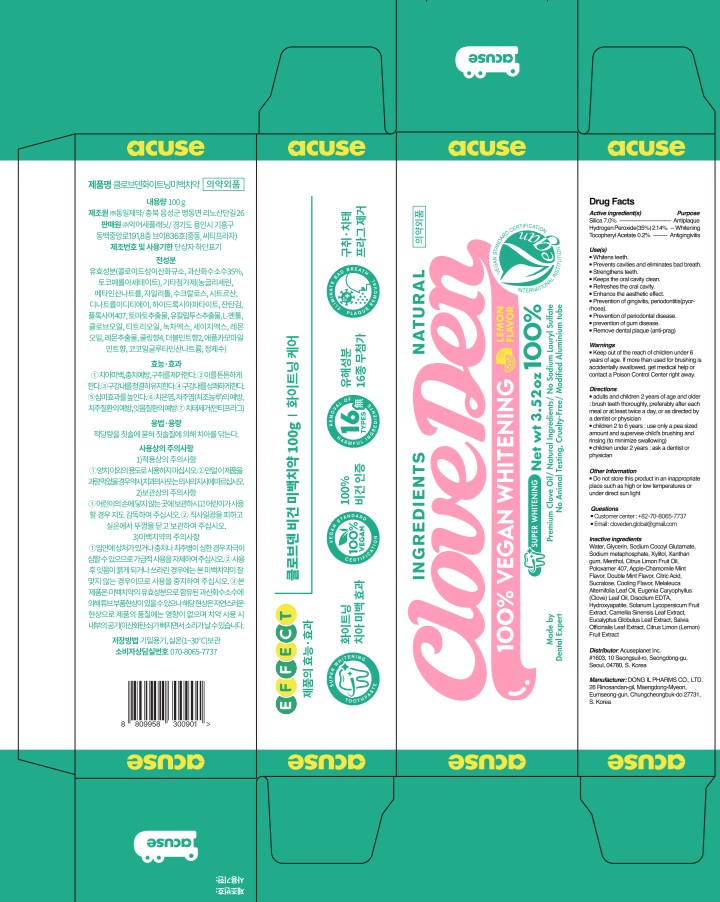 DRUG LABEL: Cloveden Vegan Whitening Tooth
NDC: 73242-1114 | Form: PASTE, DENTIFRICE
Manufacturer: DONG IL PHARMS CO.,LTD
Category: otc | Type: HUMAN OTC DRUG LABEL
Date: 20250926

ACTIVE INGREDIENTS: HYDROGEN PEROXIDE 2.14 g/100 g; .ALPHA.-TOCOPHEROL ACETATE 0.2 g/100 g; SILICON DIOXIDE 7 g/100 g
INACTIVE INGREDIENTS: GLYCERIN; SODIUM METAPHOSPHATE; WATER; SODIUM COCOYL GLUTAMATE

Active ingredient(s)

Silica 7.0%

Hydrogen Peroxide(35%) 2.14%

Tocopheryl Acetate 0.2%

Purpose

Antiplaque

Whitening

Antigingivitis

INDICATIONS AND USAGE

Use(s)

■ Whitens teeth.

■ Prevents cavities and eliminates bad breath.

■ Strengthens teeth.

■ Keeps the oral cavity clean.

■ Refreshes the oral cavity.

■ Enhance the aesthetic effect.

■ Prevention of gingivitis, periodontitis (pyorrhoea).

■ Prevention of periodontal disease.

■ prevention of gum disease.

■ Remove dental plaque (anti-prag)

Warnings

■ Keep out of the reach of children under 6 years of age. If more than used for brushing is accidentally swallowed, get medical help or contact a Poison Control Center right away.

Keep out of reach of children

Directions

■ adults and children 2 years of age and older : brush teeth thoroughly, preferably after each meal or at least twice a day, or as directed by a dentist or physician

■ children 2 to 6 years : use only a pea sized amount and supervise child's brushing and rinsing (to minimize swallowing)

■ children under 2 years : ask a dentist or physician

Other Information

■ Do not store this product in an inappropriate place such as high or low temperatures or under direct sun light

Questions

■ https://acuseplanet.cafe24.com/shop2/
■ Customer center : 070-8065-7737

Inactive ingredients

Water, Glycerin, Sodium Cocoyl Glutamate, Sodium metaphosphate, Xylitol, Xanthan gum, Menthol, Citrus Limon Fruit Oil, Poloxamer 407, Apple-Chamomile Mint Flavor, Double Mint Flavor, Citric Acid, Sucralose, Cooling Flavor, Melaleuca Alternifolia Leaf Oil, Eugenia Caryophyllus (Clove) Leaf Oil, Disodium EDTA, Hydroxyapatite, Solanum Lycopersicum Fruit Extract, Camellia Sinensis Leaf Extract, Eucalyptus Globulus Leaf Extract, Salvia Officinalis Leaf Extract, Citrus Limon (Lemon) Fruit Extract